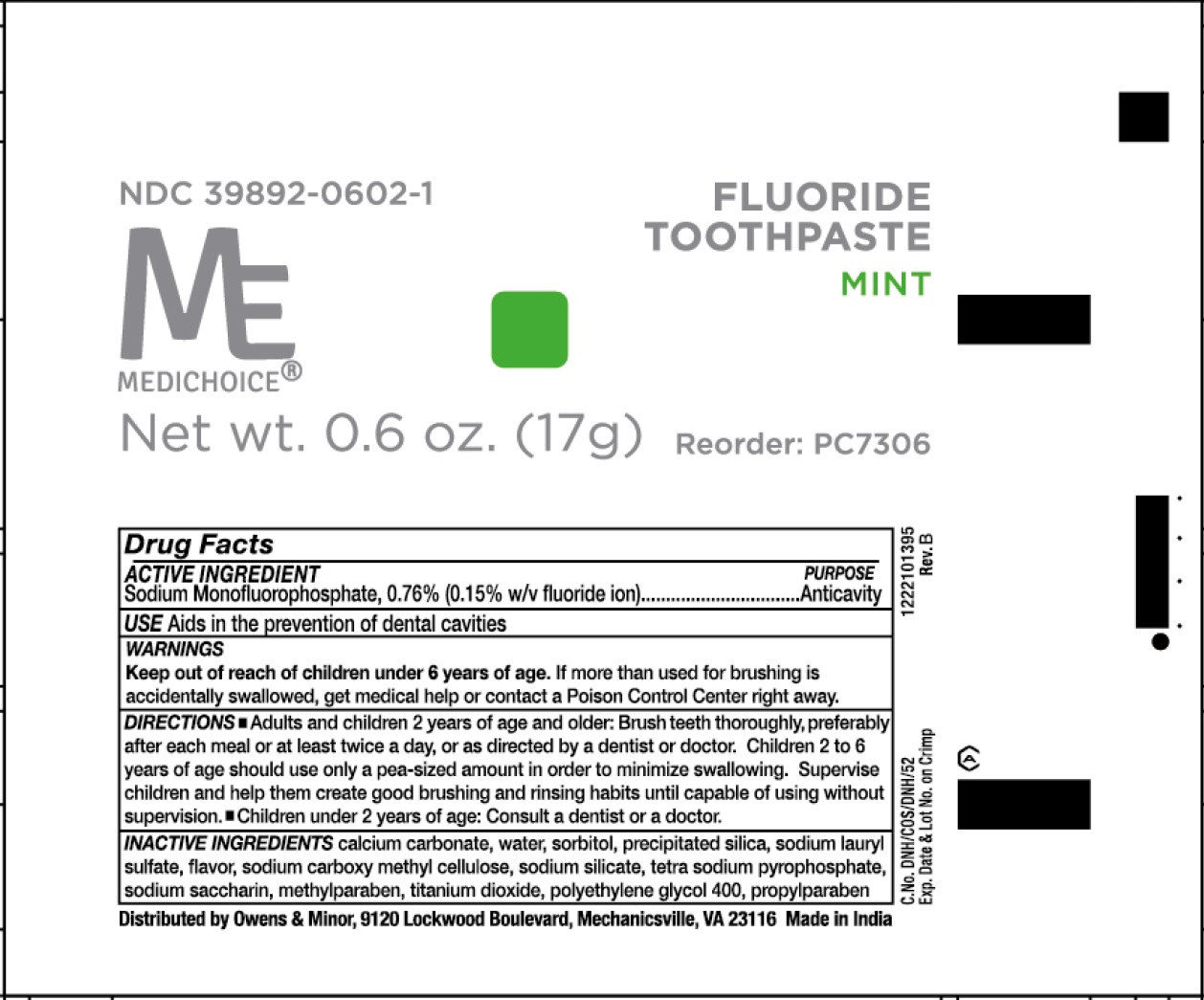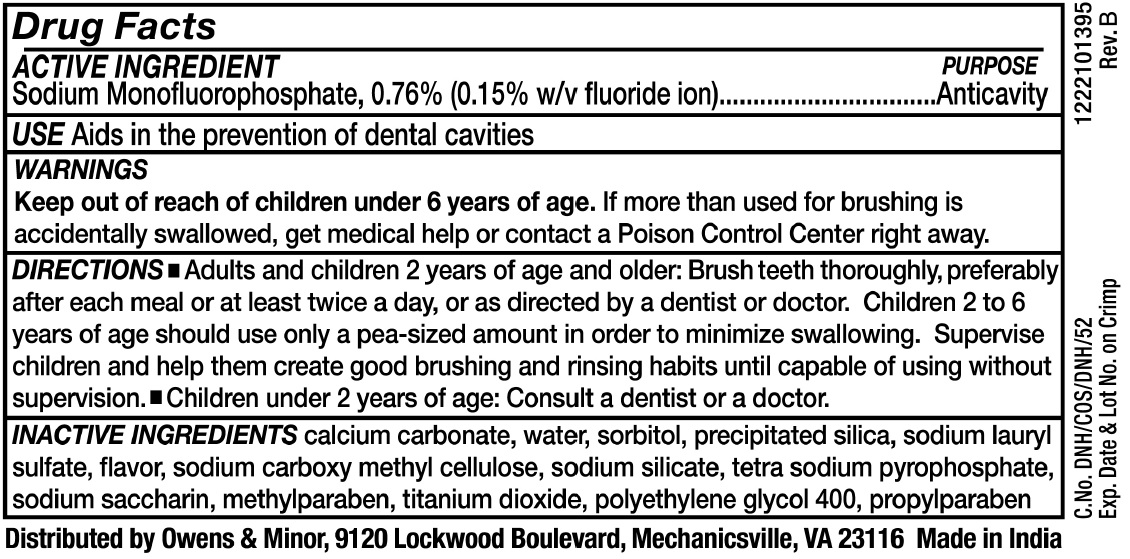 DRUG LABEL: MediChoice Fluoride
NDC: 39892-0602 | Form: PASTE, DENTIFRICE
Manufacturer: O&M HALYARD, INC.
Category: otc | Type: HUMAN OTC DRUG LABEL
Date: 20251009

ACTIVE INGREDIENTS: SODIUM MONOFLUOROPHOSPHATE 7.6 mg/1 g
INACTIVE INGREDIENTS: CALCIUM CARBONATE; WATER; SORBITOL; SILICON DIOXIDE; SODIUM LAURYL SULFATE; CARBOXYMETHYLCELLULOSE SODIUM; SODIUM SILICATE; SODIUM PYROPHOSPHATE; SACCHARIN SODIUM; METHYLPARABEN; TITANIUM DIOXIDE; POLYETHYLENE GLYCOL 400; PROPYLPARABEN

MediChoice Fluoride Toothpaste

ACTIVE INGREDIENT

Sodium Monoflurophosphate - 0.76% (0.15% w/v fluoride ion)

PURPOSE

Anticavity

USE

Aids in the prevention of dental cavities

WARNINGS

Keep out of reach of children under 6 years of age.

If more than used for brushing is accidentally swallowed, get medical help or contact a Poison Control Center right away.

DIRECTIONS

- Adults and children 2 years of age and olden Brush teeth thoroughly, preferably after each meal or at least twice a day, or as directed by a dentist or doctor. Children 2 to 6 years of age should use only a pea-sized amount in order to minimize swallowing. Supervise children and help them create good brushing and rinsing habits until capable of using without supervision.
- Children under 2 years of age: Consult a dentist or a doctor.

INACTIVE INGREDIENTS

CALCIUM CARBONATE,WATER,SORBITOL,PRECIPITATED SILICA,SODIUM LAURYL SULFATE, SODIUM CARBOXY METHYL CELLULOSE, SODIUM SILICATE TETRA SODIUM PYROPHOSPHATE, SODIUM SACCHARIN,METHYLPARABEN,TITANIUM DIOXIDE POLYETHYLENE GLYCOL 400,PROPYLPARABEN